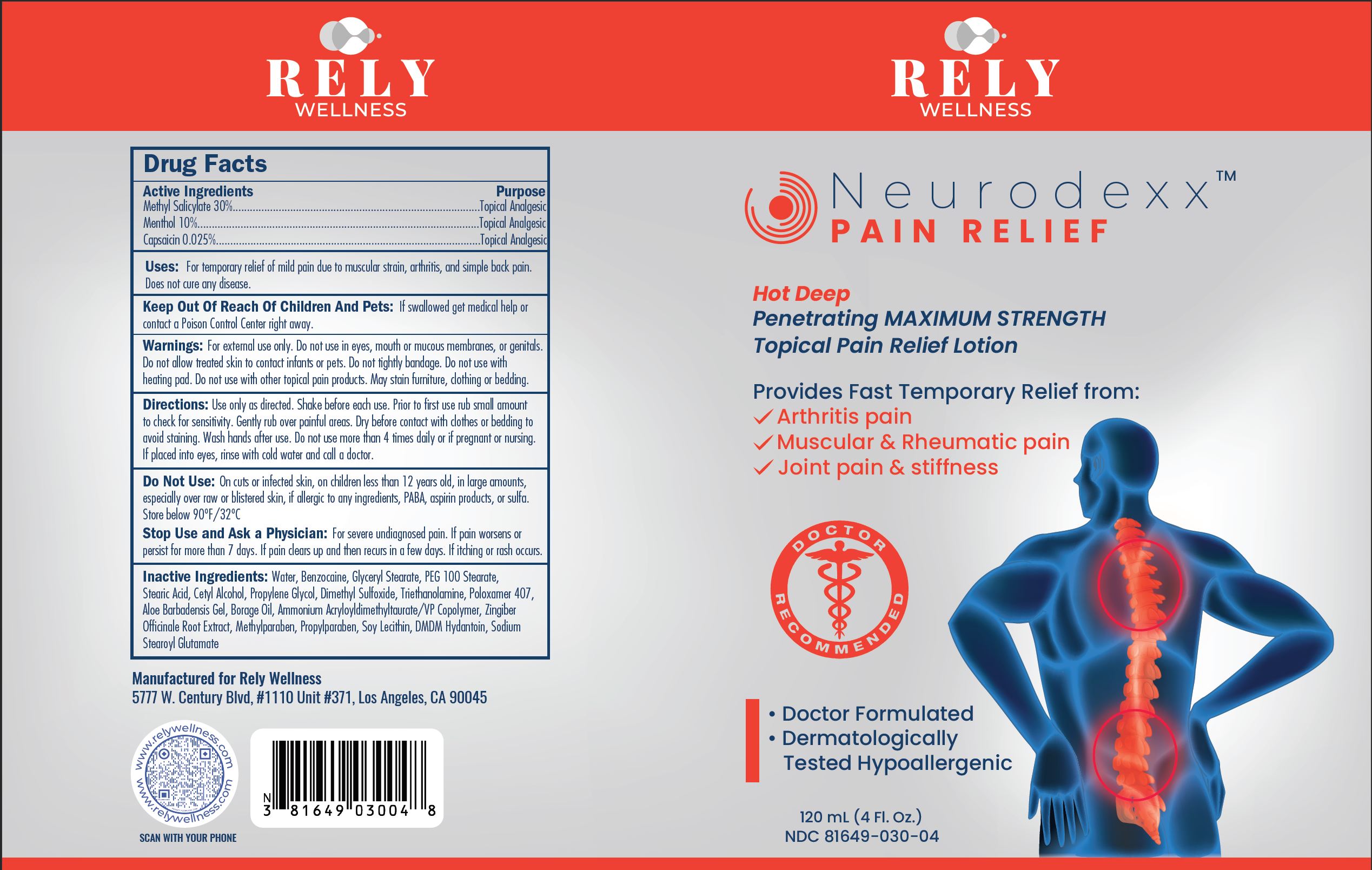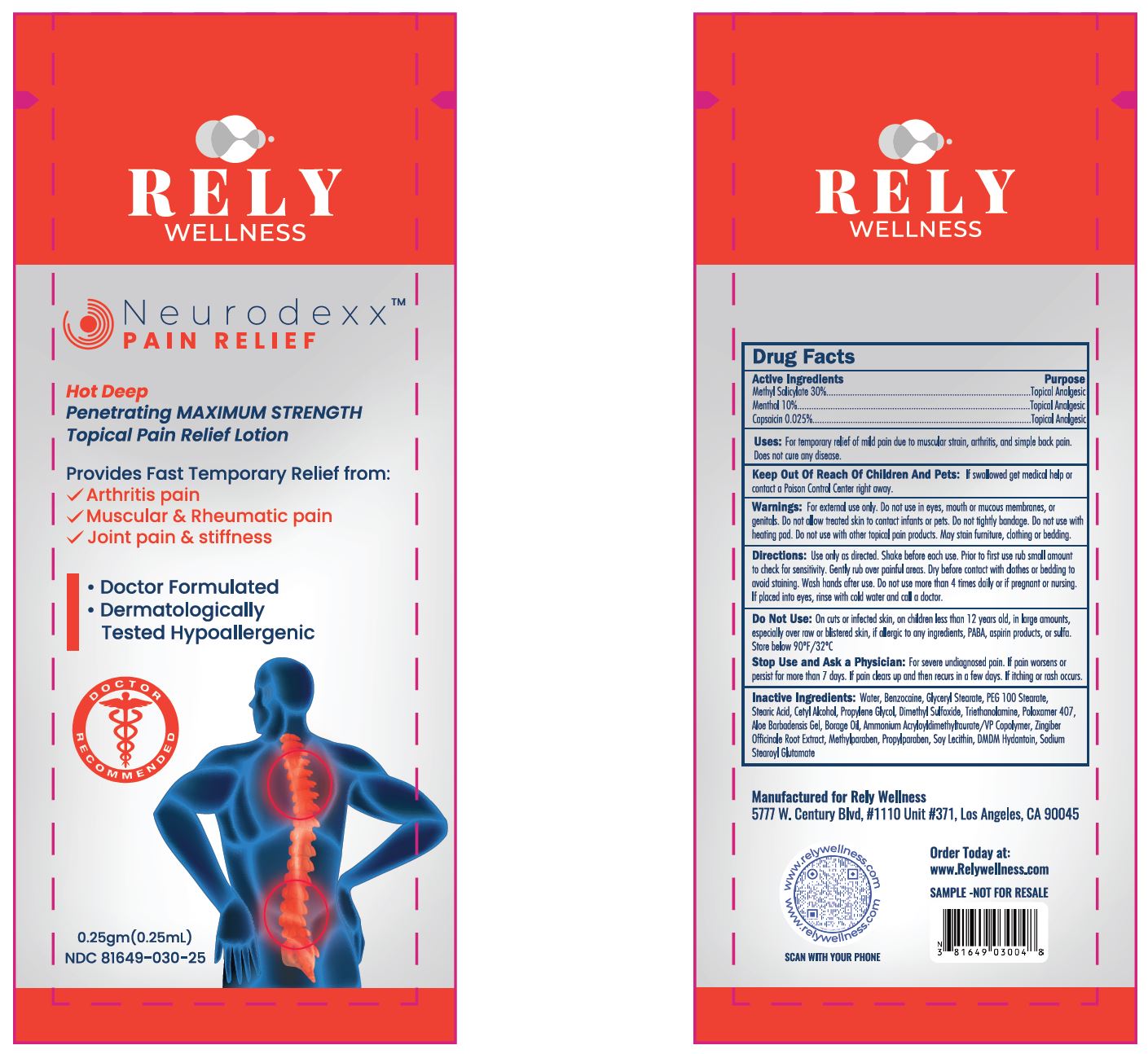 DRUG LABEL: Neurodexx
NDC: 81649-030 | Form: LOTION
Manufacturer: Rely Wellness
Category: otc | Type: HUMAN OTC DRUG LABEL
Date: 20230116

ACTIVE INGREDIENTS: METHYL SALICYLATE 18 g/60 mL; MENTHOL 6 g/60 mL; CAPSAICIN 0.015 g/60 mL
INACTIVE INGREDIENTS: WATER; BENZOCAINE; GLYCERYL MONOSTEARATE; PEG-100 STEARATE; STEARIC ACID; PROPYLENE GLYCOL; CETYL ALCOHOL; DIMETHYL SULFOXIDE; POLOXAMER 407; ALOE VERA LEAF; BORAGE SEED OIL; AMMONIO METHACRYLATE COPOLYMER TYPE A; GINGER; LECITHIN, SOYBEAN; METHYLPARABEN; PROPYLPARABEN; DMDM HYDANTOIN; SODIUM STEAROYL GLUTAMATE; TROLAMINE

Neurodexx™ Pain Relief

ACTIVE INGREDIENTS

Methyl Salicylate 30%
Menthol 10%
Capsaicin 0.025%

Purpose

Topical Analgesic

Uses:

For temporary relief of mild pain due to muscular strain, arthritis, and simple back pain. Does not cure any disease.

Keep Out Of Reach Of Children And Pets:

If swallowed get medical help or contact a Poison Control Center right away.

Warnings:

For external use only. Do not use in eyes, mouth or mucous membranes, or genitals. Do not allow treated skin to contact infants or pets. Do not tightly bandage. Do not use with heating pad. Do not use with other topical pain products. May stain furniture, clothing or bedding.

Directions:

Use only as directed. Shake before each use. Prior to first use rub small amount to check for sensitivity. Gently rub over painful areas. Dry before contact with clothes or bedding to avoid staining. Wash hands after use. Do not use more than 4 times daily or if pregnant or nursing. If swallowed, call poison control. If placed into eyes, rinse with cold water and call a doctor.

Do Not Use:

On cuts or infected skin, on children less than 12 years old, in large amounts, especially over raw or blistered skin, if allergic to any ingredients, PABA, aspirin products, or sulfa. Store below 90°F/32°C.

Stop Use and Ask a Physician:

For severe undiagnosed pain. If pain worsens or persist for more than 7 days. If pain clears up and then recurs in a few days. If itching or rash occurs.

Inactive Ingredients:

Water, Benzocaine, Glyceryl Stearate, PEG 100 Stearate, Stearic Acid, Cetyl Alcohol, Propylene Glycol, Dimethyl Sulfoxide, Triethanolamine, Poloxamer 407, Aloe Barbadensis Gel, Borage Oil, Ammonium Acryloyldimethyltaurate/VP Copolymer, Zingiber Officinale Root Extract, Methylparaben, Propylparaben, Soy Lecithin, DMDM Hydantoin, Sodium Stearoyl Glutamate

Manufactured for: Rely Wellness
5777 W. Century Blvd, #1100 Unit #371, Los Angeles, CA 90045

Neurodexx™ Pain Relief

Hot Deep

Penetrating MAXIMUM STRENGTH

Topical Pain Relief Lotion

Provides Fast Temporary Relief from:

- Arthritis pain
- Muscular & Rheumetric pain
- Joint pain & stifness

Doctor Recommended

- Doctor Formulated
- Dermatologically Tested Hypoallergenic

120 ml (4 fl oz)
NDC 81649-030-04

0.25gm (0.25 ml)

NDC 81649-030-25